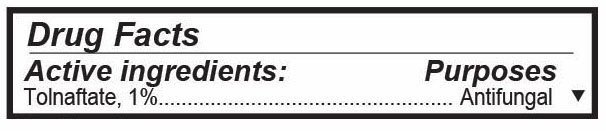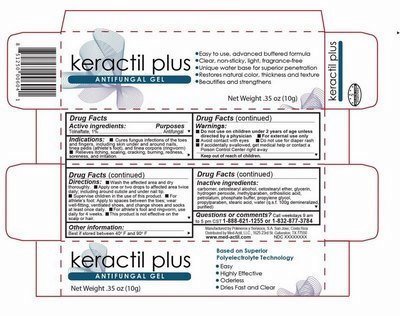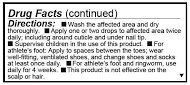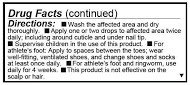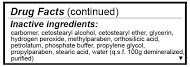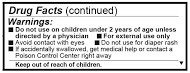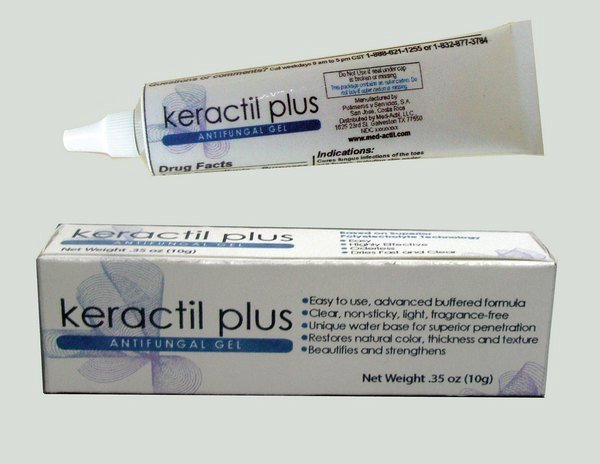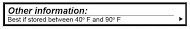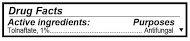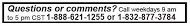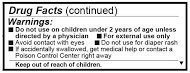 DRUG LABEL: KERACTIL
NDC: 69492-014 | Form: GEL
Manufacturer: POLIMEROS Y SERVICIOS S.A.
Category: otc | Type: HUMAN OTC DRUG LABEL
Date: 20190305

ACTIVE INGREDIENTS: TOLNAFTATE 10 mg/1 g
INACTIVE INGREDIENTS: CARBOXYPOLYMETHYLENE; CETOSTEARYL ALCOHOL; HYDROGEN PEROXIDE; METHYLPARABEN; ORTHOSILICIC ACID; POLYOXYL 20 CETOSTEARYL ETHER; PROPYLPARABEN; SODIUM PHOSPHATE, DIBASIC; WATER

Submission for KERACTIL Plus Topical Antifungal Gel

Representative sample image of carton/container label

General view of box content of labeling

Caja con cambios Keractil Plus.jpg

Representative sample image of carton/container label

Keractil Fondo gris.jpg

Detail showing Active Ingredient from package

Information shown both on container label and package

Active Ingredients- Keractil plus.jpg

Detail showing Inctive Ingredient from package

Infiomaion shown both on content of label and package

Inactive ingredients.jpg

Detail showing Purpose within Active Ingredients from package

Information shown both on container label and package

Purpose.jpg

Detail showing Instructions for use and named Uses from package

Ibformation shown both on container label and package

Directions.jpg

Detail showing Dosage and Administration within Directions from package

Information shown both on container label and package

Dosage and administration.jpg

Detail showing Warnings from package

Information shown both on cintainer label and package

Warnings-.jpg

Detail showing Keep Out of Reach of Children within Warnings from package

Information shown both on cobtainer label and package

Keep out of reach of children.jpg

Detail showing Questions from package

Information shown both on container label and package

Questions Keractil Plus.jpg

Detail showing Other Safety Information from package

Ibformation shown both on container label and package

Other information Keractil plus.jpg